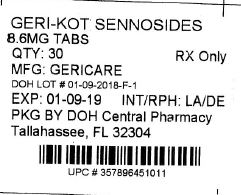 DRUG LABEL: Geri-kot
                
NDC: 53808-1110 | Form: TABLET
Manufacturer: DOH CENTRAL PHARMACY
Category: otc | Type: HUMAN OTC DRUG LABEL
Date: 20190117

ACTIVE INGREDIENTS: SENNOSIDES 8.6 mg/1 1
INACTIVE INGREDIENTS: CELLULOSE, MICROCRYSTALLINE; CROSCARMELLOSE SODIUM; ANHYDROUS DIBASIC CALCIUM PHOSPHATE; MAGNESIUM SILICATE; MAGNESIUM STEARATE; MINERAL OIL; POLYETHYLENE GLYCOL, UNSPECIFIED; HYPROMELLOSE, UNSPECIFIED

Active ingredient (in each tablet)

Sennosides 8.6 mg

Purpose

Laxative

Uses

- relieves occasional constipation (irregularity)

- generally produces bowel movement in 6 to 12 hours

Warnings

Do not use for more than 1 week unless directed by a doctor.

Ask a doctor before use if you
• have abdominal pain, nausea or vomiting
• have noticed a sudden change in bowel habits that lasts over 2 weeks

Stop use and ask a doctor if
• you have no bowel movement within 12 hours
• you have rectal bleeding
These could be signs of a serious condition.

If pregnant or breast-feeding, ask a health professional before use.

Keep out of reach of children. In case of overdose, get medical help or contact a Poison Control Center right away.

Directions

• do not exceed 8 tablets in 24 hours

Age | Starting Dose | Maximum Dose
adults and children 12 years of age and older | 2 tablets once a day preferably at bedtime; increase as needed, or as directed by a doctor | 4 tablets in the morning and 4 tablets at bedtime
children under 12 years | ask a doctor

Other information

• each tablet contains: calcium 20 mg
• store at room temperature

This Product was Repackaged By:

DOH CENTRAL PHARMACY
104 HAMILTON PARK DR # 2
TALLAHASSEE, FL 32304
USA

Inactive ingredients

cellulose, croscarmellose sodium, dicalcium phosphate, hypromellose, magnesium silicate, magnesium stearate, mineral oil, PEG.

PACKAGE LABEL

Label Image for 53808-1110
8.6mg